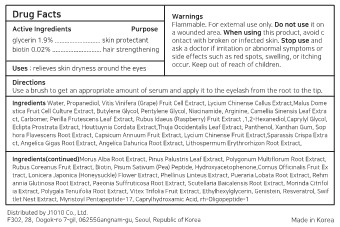 DRUG LABEL: Dr. Zonskin Nunssup Jara
NDC: 82934-301 | Form: LIQUID
Manufacturer: J 1010 Co., Ltd.
Category: otc | Type: HUMAN OTC DRUG LABEL
Date: 20220825

ACTIVE INGREDIENTS: GLYCERIN 1.9 g/100 mL; BIOTIN 0.02 g/100 mL
INACTIVE INGREDIENTS: ACENEURAMIC ACID; MYRISTOYL PENTAPEPTIDE-4; PROPANEDIOL; WINE GRAPE; APPLE; LYCIUM CHINENSE WHOLE; WATER; BUTYLENE GLYCOL; PENTYLENE GLYCOL; NIACINAMIDE; ARGININE; GREEN TEA LEAF; PERILLA FRUTESCENS LEAF; RASPBERRY; 1,2-HEXANEDIOL; CAPRYLYL GLYCOL; ECLIPTA PROSTRATA LEAF; HOUTTUYNIA CORDATA FLOWERING TOP; THUJA OCCIDENTALIS LEAF; PANTHENOL; XANTHAN GUM; SOPHORA FLAVESCENS ROOT; PAPRIKA; LYCIUM CHINENSE FRUIT; SPARASSIS CRISPA WHOLE; ANGELICA GIGAS ROOT; ANGELICA DAHURICA ROOT; LITHOSPERMUM ERYTHRORHIZON ROOT; MORUS ALBA ROOT; PINUS PALUSTRIS LEAF; REYNOUTRIA MULTIFLORA ROOT; RUBUS COREANUS FRUIT; CARBOMER HOMOPOLYMER, UNSPECIFIED TYPE; PEA; HYDROXYACETOPHENONE; CORNUS OFFICINALIS FRUIT; LONICERA JAPONICA FLOWER; PHELLINUS LINTEUS WHOLE; PUERARIA MONTANA VAR. LOBATA ROOT; REHMANNIA GLUTINOSA ROOT; PAEONIA X SUFFRUTICOSA ROOT; SCUTELLARIA BAICALENSIS ROOT; MORINDA CITRIFOLIA LEAF; POLYGALA TENUIFOLIA ROOT; VITEX TRIFOLIA FRUIT; ETHYLHEXYLGLYCERIN; GENISTEIN; RESVERATROL; CAPRYLHYDROXAMIC ACID; NEPIDERMIN

82934-301 Dr. Zonskin Nunssup Jara

Active ingredients

glycerin 1.9%

biotin 0.02%

Purpose

skin protectant and hair strengthening

Use

relieves skin dryness around the eyes

Warnings

Do not use it on a wounded area.

Warnings

When using this product, avoid c ontact with broken or infected skin.

Warnings

Stop use and ask a doctor if irritation or abnormal symptoms or side effects such as red spots, swelling, or itching occur.

Warnings

Flammable. For external use only.

Warnings

Keep out of reach of children.

Directions

Use a brush to get an appropriate amount of serum and apply it to the eyelash from the root to the tip.

Inactive ingredients

Water, Propanediol, Vitis Vinifera (Grape) Fruit Cell Extract, Lycium Chinense Callus Extract,Malus Dome stica Fruit Cell Culture Extract, Butylene Glycol, Pentylene Glycol, Niacinamide, Arginine, Camellia Sinensis Leaf Extra ct, Carbomer, Perilla Frutescens Leaf Extract, Rubus Idaeus (Raspberry) Fruit Extract ,1,2-Hexanediol,Caprylyl Glycol, Eclipta Prostrata Extract, Houttuynia Cordata Extract,Thuja Occidentalis Leaf Extract, Panthenol, Xanthan Gum, Sop hora Flavescens Root Extract, Capsicum Annuum Fruit Extract, Lycium Chinense Fruit Extract,Sparassis Crispa Extra ct, Angelica Gigas Root Extract, Angelica Dahurica Root Extract, Lithospermum Erythrorhizon Root Extract,

Morus Alba Root Extract, Pinus Palustris Leaf Extract, Polygonum Multiflorum Root Extract, Rubus Coreanus Fruit Extract, Biotin, Pisum Sativum (Pea) Peptide, Hydroxyacetophenone,Cornus Officinalis Fruit Ex tract, Lonicera Japonica (Honeysuckle) Flower Extract, Phellinus Linteus Extract, Pueraria Lobata Root Extract, Rehm annia Glutinosa Root Extract, Paeonia Suffruticosa Root Extract, Scutellaria Baicalensis Root Extract, Morinda Citrifol ia Extract, Polygala Tenuifolia Root Extract, Vitex Trifolia Fruit Extract, Ethylhexylglycerin, Genistein, Resveratrol, Swif tlet Nest Extract, Myristoyl Pentapeptide-17, Caprylhydroxamic Acid, rh-Oligopeptide-1